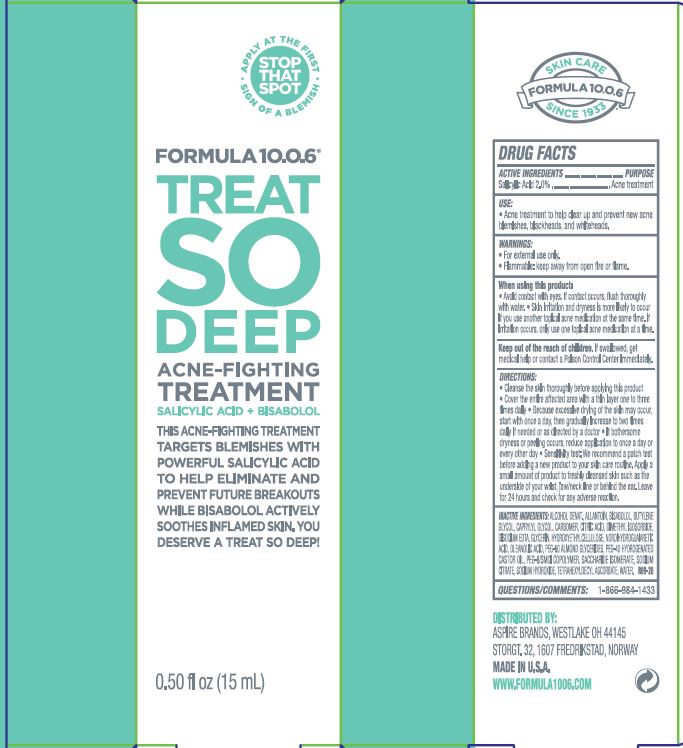 DRUG LABEL: TREAT SO DEEP ACNE-FIGHTING TREATMENT
NDC: 70626-106 | Form: GEL
Manufacturer: ASPIRE BRANDS INC
Category: otc | Type: HUMAN OTC DRUG LABEL
Date: 20241206

ACTIVE INGREDIENTS: SALICYLIC ACID 2 g/100 mL
INACTIVE INGREDIENTS: ALCOHOL; ALLANTOIN; .ALPHA.-BISABOLOL, (+)-; BUTYLENE GLYCOL; CAPRYLYL GLYCOL; CARBOMER HOMOPOLYMER, UNSPECIFIED TYPE; ANHYDROUS CITRIC ACID; DIMETHYL ISOSORBIDE; EDETATE DISODIUM; GLYCERIN; HYDROXYETHYL CELLULOSE, UNSPECIFIED; NORDIHYDROGUAIARETIC ACID, (+/-)-; OLEANOLIC ACID; PEG-60 ALMOND GLYCERIDES; POLYOXYL 40 HYDROGENATED CASTOR OIL; PEG-8/SMDI COPOLYMER; SACCHARIDE ISOMERATE; SODIUM CITRATE, UNSPECIFIED FORM; SODIUM HYDROXIDE; TETRAHEXYLDECYL ASCORBATE; WATER

ASPIRE BRANDS - FORMULA 10.0.6 TREAT SO DEEP ACNE-FIGHTING TREATMENT (70626-106)

ACTIVE INGREDIENT

SALICYLIC ACID 2%

PURPOSE

ACNE TREATMENT

USE

ACNE TREATMENT TO HELP CLEAR UP AND PREVENT NEW ACNE BLEMISHES, BLACKHEADS, AND WHITEHEADS.

WARNINGS

- FOR EXTERNAL USE ONLY
- FLAMMABLE: KEEP AWAY FROM OPEN FIRE OR FLAME.

WHEN USING THIS PRODUCT:

- AVOID CONTACT WITH EYES. IF CONTACT OCCURS, FLUSH THOROUGHLY WITH WATER.
- SKIN IRRITATION AND DRYNESS IS MORE LIKELY TO OCCUR IF YOU USE ANOTHER TOPICAL ACNE MEDICATION AT THE SAME TIME. IF IRRITATION OCCURS, ONLY USE ONE TOPICAL ACNE MEDICATION AT A TIME.

KEEP OUT OF REACH OF CHILDREN. IF SWALLOWED, GET MEDICAL HELP OR CONTACT A POISON CONTROL CENTER RIGHT AWAY.

DIRECTIONS

- CLEAN THE SKIN THOROUGHLY BEFORE APPLYING THIS PRODUCT.
- COVER THE ENTIRE AFFECTED AREA WITH A THIN LAYER ONE TO THREE TIMES DAILY.
- BECAUSE EXCESSIVE DRYING OF THE SKIN MAY OCCUR, START WITH ONCE A DAY, THEN GRADUALLY INCREASE TO TWO TIMES DAILY IF NEEDED OR AS DIRECTED BY A DOCTOR.
- IF BOTHERSOME DRYNESS OR PEELING OCCURS, REDUCE APPLICATION TO ONCE A DAY OR EVERY OTHER DAY
- SENSITIVITY TEST: WE RECOMMEND A PATCH TEST BEFORE ADDING A NEW PRODUCT TO YOUR SKIN CARE ROUTINE. APPLY A SMALL AMOUNT OF PRODUCT TO FRESHLY CLEANSED SKIN SUCH AS THE UNDERSIDE OF YOUR WRIST, JAW/NECK LINE OR BEHIND THE EAR. LEAVE FOR 24 HOURS AND CHECK FOR ANY ADVERSE REACTION.

INACTIVE INGREDIENTS

ALCOHOL DENAT., ALLANTOIN, BISABOLOL, BUTYLENE GLYCOL, CAPRYLYL GLYCOL, CARBOMER, CITRIC ACID, DIMETHYL ISOSORBIDE, DISODIUM EDTA, GLYCERIN, HYDROXYETHYLCELLULOSE, NORDIHYDROGUAIARETIC ACID, OLEANOLIC ACID, PEG-60 ALMOND GLYCERIDES, PEG-40 HYDROGENATED CASTOR OIL, PEG-8/SMDI COPOLYMER, SACCHARIDE ISOMERATE, SODIUM CITRATE, SODIUM HYDROXIDE, TETRAHEXYLDECYL ASCORBATE, WATER.

QUESTIONS/COMMENTS:

1-866-984-1433